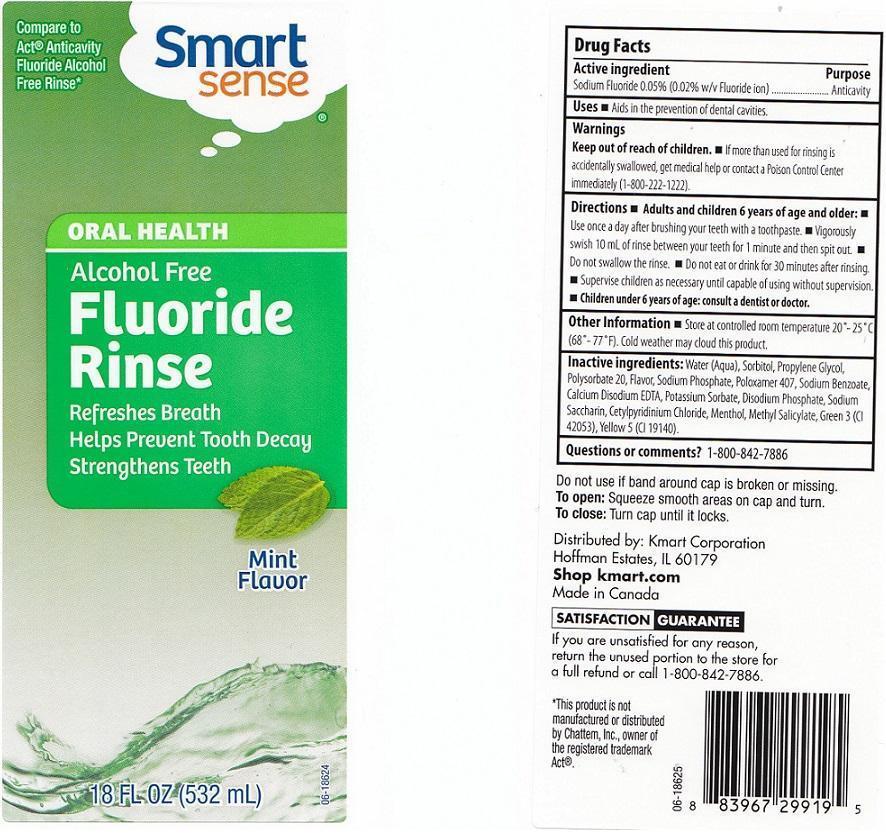 DRUG LABEL: SMART SENSE
NDC: 49738-554 | Form: LIQUID
Manufacturer: KMART CORPORATION
Category: otc | Type: HUMAN OTC DRUG LABEL
Date: 20130509

ACTIVE INGREDIENTS: SODIUM FLUORIDE 0.5 mg/1 mL
INACTIVE INGREDIENTS: WATER; SORBITOL; PROPYLENE GLYCOL; POLYSORBATE 20; SODIUM PHOSPHATE; POLOXAMER 407; SODIUM BENZOATE; EDETATE CALCIUM DISODIUM ANHYDROUS; POTASSIUM SORBATE; SODIUM PHOSPHATE, DIBASIC, ANHYDROUS; SACCHARIN SODIUM; CETYLPYRIDINIUM CHLORIDE; MENTHOL; METHYL SALICYLATE; FD&C GREEN NO. 3; FD&C YELLOW NO. 5

DRUG FACTS

ACTIVE INGREDIENT

SODIUM FLUORIDE 0.05% (0.02% W/V FLUORIDE ION)

PURPOSE

ANTICAVITY

USES

AIDS IN THE PREVENTION OF DENTAL CAVITIES.

WARNINGS

KEEP OUT OF REACH OF CHILDREN. IF MORE THAN USED FOR RINSING IS ACCIDENTALLY SWALLOWED, GET MEDICAL HELP OR CONTACT A POISON CONTROL CENTER IMMEDIATELY (1-800-222-1222).

KEEP OUT OF REACH OF CHILDREN.

IF MORE THAN USED FOR RINSING IS ACCIDENTALLY SWALLOWED, GET MEDICAL HELP OR CONTACT A POISON CONTROL CENTER IMMEDIATELY (1-800-222-1222).

DIRECTIONS

ADULTS AND CHILDREN 6 YEARS OF AGE AND OLDER: USE ONCE A DAY AFTER BRUSHING YOUR TEETH WITH A TOOTHPASTE. VIGOROUSLY SWISH 10 ML OF RINSE BETWEEN YOUR TEETH FOR 1 MINUTE AND THEN SPIT OUT. DO NOT SWALLOW THE RINSE. DO NOT EAT OR DRINK FOR 30 MINUTES AFTER RINSING. SUPERVISE CHILDREN AS NECESSARY UNTIL CAPABLE OF USING WITHOUT SUPERVISION. CHILDREN UNDER 6 YEARS OF AGE: CONSULT A DENTIST OR DOCTOR.

OTHER INFORMATION

STORE AT CONTROLLED ROOM TEMPERATURE 20-25C (68-77F). COLD WEATHER MAY CLOUD THIS PRODUCT.

INACTIVE INGREDIENTS:

WATER (AQUA), SORBITOL, PROPYLENE GLYCOL, POLYSORBATE 20, FLAVOR, SODIUM PHOSPHATE, POLOXAMER 407, SODIUM BENZOATE, CALCIUM DISODIUM EDTA, POTASSIUM SORBATE, DISODIUM PHOSPHATE, SODIUM SACCHARIN, CETYLPYRIDINIUM CHLORIDE, MENTHOL, METHYL SALICYLATE, GREEN 3 (CI 42053), YELLOW 5 (CI 19140).

QUESTIONS OR COMMENTS?

1-800-842-7886